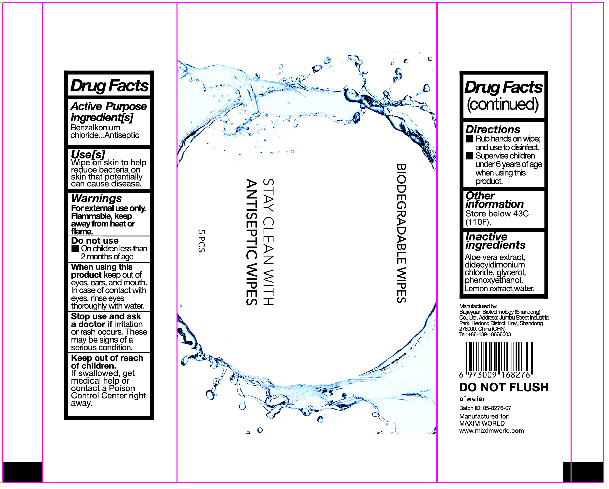 DRUG LABEL: antiseptic wipes
NDC: 55490-031 | Form: CLOTH
Manufacturer: Baijieyuan Biotechnology (Shandong) Co., Ltd.
Category: otc | Type: HUMAN OTC DRUG LABEL
Date: 20210421

ACTIVE INGREDIENTS: BENZALKONIUM CHLORIDE 0.54 g/1 1
INACTIVE INGREDIENTS: DIDECYLDIMONIUM CHLORIDE; LEMON; ALOE VERA LEAF; GLYCERIN; WATER; PHENOXYETHANOL

Other information

Store below 110°F (43°C)

INACTIVE INGREDIENT

Glycerol

Aloe vera extract

Pure water

Didecyldimonium chloride

Phenoxyethanol

Lemon extract

Use

Wipe on skin to help reduce bacteria on skin that potentially can cause disease.

ACTIVE INGREDIENT

Benzalkonium chloride

KEEP OUT OF REACH OF CHILDREN

Keep out of reachof children.lf swallowed, get medical help or contact a Poison Control Center right away.

PURPOSE

Antiseptic

WARNINGS

For external use only.Flammable,keep away from heat or flame.

Directions

Rub hands on wipe,and use to disnfect.

Supervise children under 6 years of age when using this product.

DO NOT USE

On childiren less than 2 months of age

When using this product keep out of eyes, ears,and mouth.in case of contact witheyes, rinse eyes thorougly with water

Stop use and ask a doctor if iritation or rash occurs.These may be signs of a serious condition.